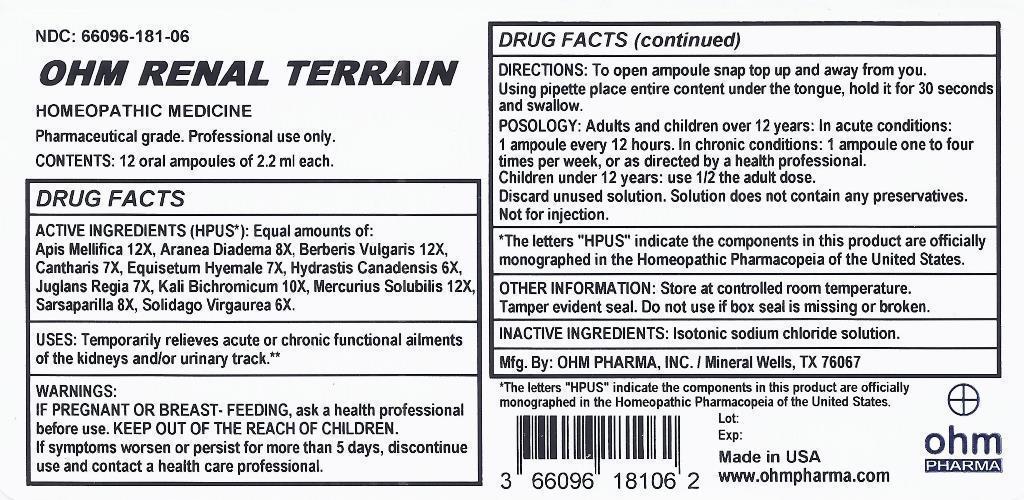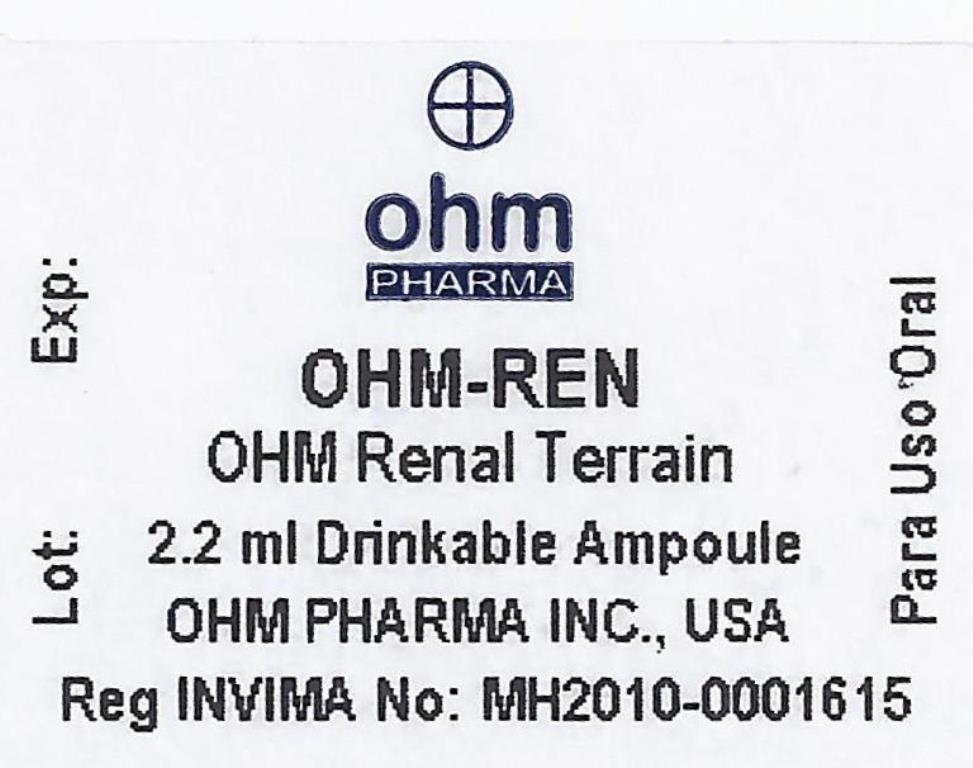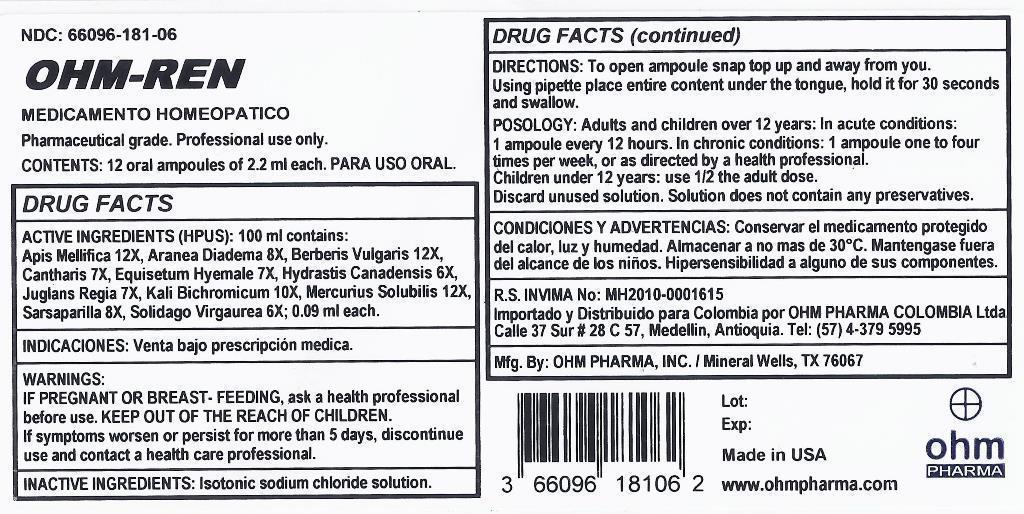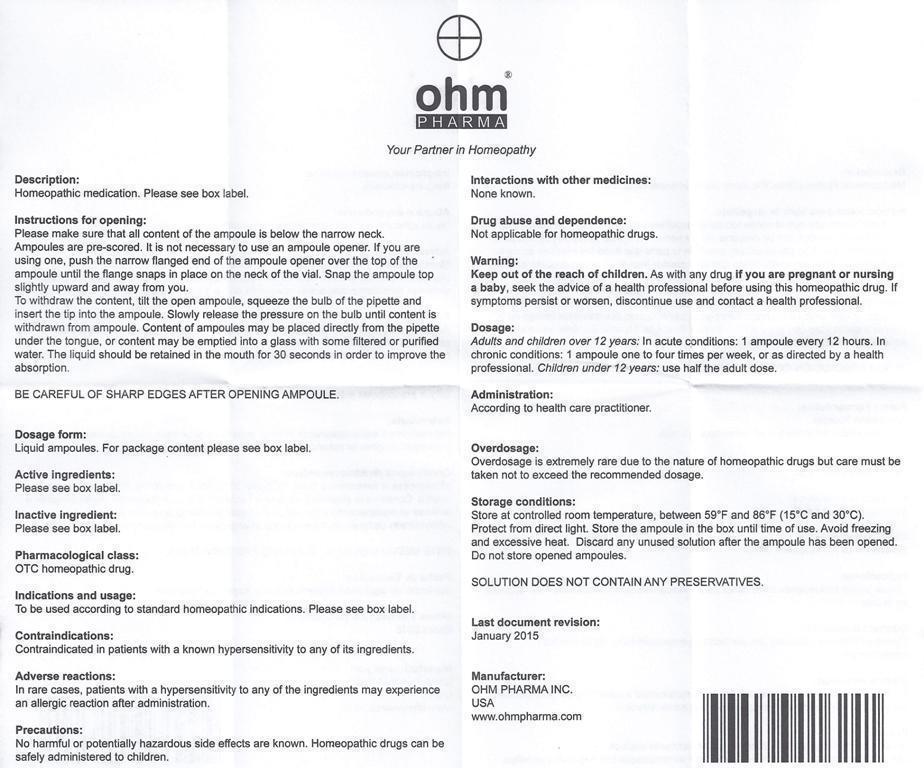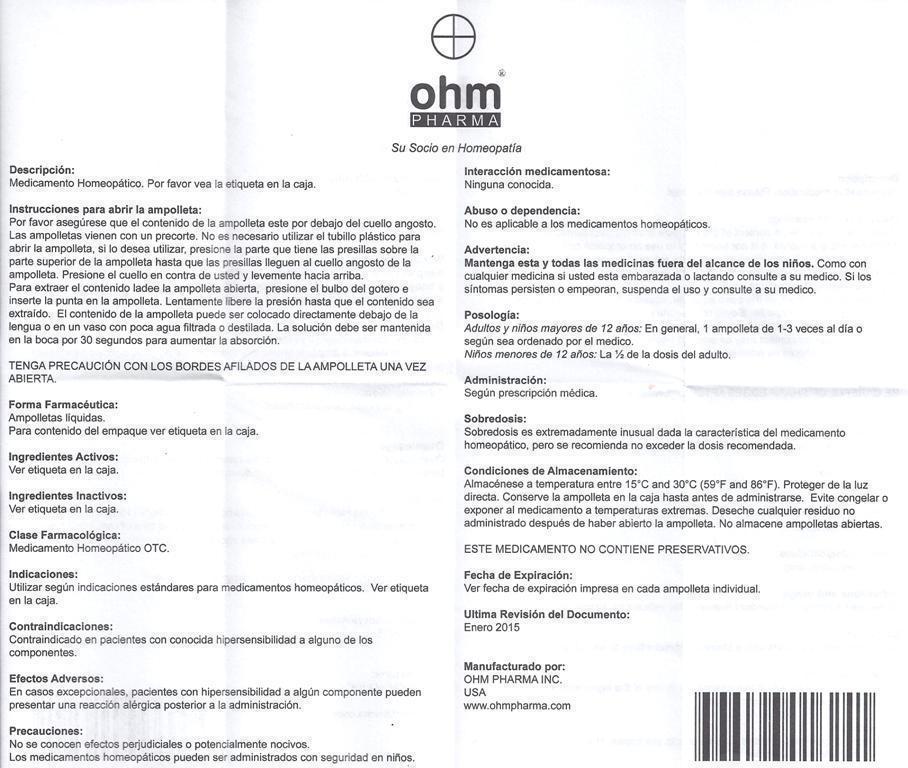 DRUG LABEL: OHM RENAL TERRAIN
NDC: 66096-181 | Form: LIQUID
Manufacturer: OHM PHARMA INC.
Category: homeopathic | Type: HUMAN OTC DRUG LABEL
Date: 20160111

ACTIVE INGREDIENTS: APIS MELLIFERA 12 [hp_X]/1 mL; ARANEUS DIADEMATUS 8 [hp_X]/1 mL; BERBERIS VULGARIS ROOT BARK 12 [hp_X]/1 mL; LYTTA VESICATORIA 7 [hp_X]/1 mL; EQUISETUM HYEMALE 7 [hp_X]/1 mL; GOLDENSEAL 6 [hp_X]/1 mL; JUGLANS REGIA LEAF 7 [hp_X]/1 mL; POTASSIUM DICHROMATE 10 [hp_X]/1 mL; MERCURIUS SOLUBILIS 12 [hp_X]/1 mL; SMILAX REGELII ROOT 8 [hp_X]/1 mL; SOLIDAGO VIRGAUREA FLOWERING TOP 6 [hp_X]/1 mL
INACTIVE INGREDIENTS: SODIUM CHLORIDE

OHM RENAL TERRAIN

ACTIVE INGREDIENT

ACTIVE INGREDIENTS (HPUS*): Equal amounts of: Apis Mellifica 12X, Aranea Diadema 8X, Berberis Vulgaris 12X, Cantharis 7X, Equisetum Hyemale 7X, Hydrastis Canadensis 6X, Juglans Regia 7X, Kali Bichromicum 10X, Mercurius Solubilis 12X, Sarsaparilla 8X, Solidago Virgaurea 6X.

ACTIVE INGREDIENT

*The letters "HPUS" indicate the components in this product are officially monographed in the Homeopathic Pharmacopeia of the United States.

INDICATIONS AND USAGE

USES: Temporarily relieves acute or chronic functional ailments of the kidneys and/or urinary track.**

**This statement has not been evaluated by the FDA.
It is based on documented Homeopathic Materia Medica.

WARNINGS:

IF PREGNANT OR BREAST-FEEDING, ask a health professional before use. If symptoms worsen or persist for more than 5 days, discontinue use and contact a health care professional.

KEEP OUT OF THE REACH OF CHILDREN.

DOSAGE AND ADMINISTRATION

DIRECTIONS: To open ampoule snap top up and away from you. Using pipette place entire content under the tongue, hold it for 30 seconds and swallow.

POSOLOGY: Adults and children over 12 years: In acute conditions: 1 ampoule every 12 hours. In chronic conditions: 1 ampoule one to four times per week, or as directed by a health professional.

Children under 12 years use 1/2 the adult dose.

Discard unused solution. Solution does not contain any preservatives.

Not for injection.

OTHER INFORMATION: Store at controlled room temperature. Tamper evident seal. Do not use if box seal is missing or broken.

INACTIVE INGREDIENTS: Isotonic sodium chloride solution.

QUESTIONS

Mfg. By: OHM PHARMA, INC. / Mineral Wells, TX 76067

Made in USA

www.ohmpharma.com

PURPOSE

Acute or chronic functional ailments of the kidneys and/or urinary track relief

PACKAGE LABEL

NDC: 66096-181-06

OHM RENAL TERRAIN

HOMEOPATHIC MEDICINE

Pharmaceutical Grade. Professional use only.

CONTENTS: 12 oral ampoules of 2.2 ml each.